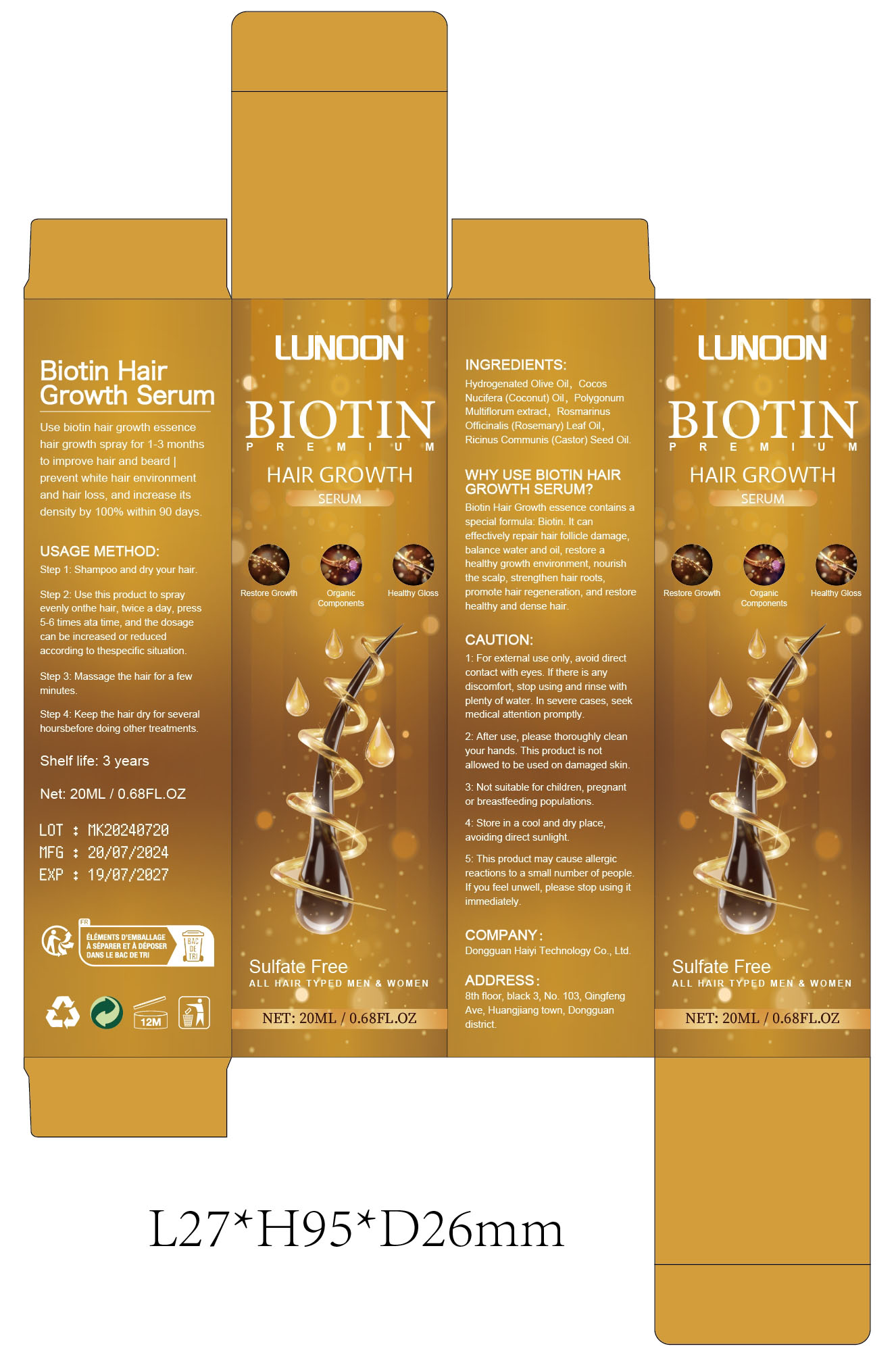 DRUG LABEL: Biotin hair growth serum
NDC: 84732-047 | Form: SPRAY
Manufacturer: Dongguan Haiyi Technology Co.,Ltd.
Category: otc | Type: HUMAN OTC DRUG LABEL
Date: 20241015

ACTIVE INGREDIENTS: HYDROGENATED OLIVE OIL 1 mg/100 mL
INACTIVE INGREDIENTS: ROSEMARY OIL; REYNOUTRIA MULTIFLORA ROOT; COCONUT OIL; CASTOR OIL

Active ingredient

Hydrogenated Olive Oil

Inactive ingredient

CocosNucifera (Coconut) Oil, PolygonumMultiflorum extract, RosmarinusOfficinalis (Rosemary) Leaf Oil,Ricinus Communis (Castor) Seed Oil

Purpose section

Biotin Hair Growth essence contains aspecial formula: Biotin. lt can effectively repair hair follicle damage,balance water and oil, restore a healthy growth environment, nourishthe scalp, strengthen hair roots,promote hair regeneration, and restore healthy and dense hair.

Warning

1: For external use only, avoid directcontact with eyes. if there is any discomfort, stop using and rinse with plenty ofwater. In severe cases, seekmedical attention promptly.
2: After use, please thoroughly cleanyour hands. This product is not allowed to be used on damaged skin.
3: Not suitable for children, pregnantor breastfeeding populations.
4: Store in a cool and dry place,avoiding direct sunlight.
5: This product may cause allergicreactions to a small number of peopleIf you feel unwell, please stop using it immediately

stop use

This product may cause allergic reactions in asmall number of people.
lf youexperience any discomfort,please stop using it immediately.

not use

This product may cause allergicreactions to a small number of peopleIf you feel unwell, please stop using itimmediately

OUT OF CHILDREN

KEEP THE PRODUCT OUT OF REACH OF CHILDREN to

HOW TO USE

Step 1: Shampoo and dry your hair.
Step 2: Use this product to sprayevenly onthe hair, twice a day, press5-6 times ata time, and the dosagecan be increased or reducedaccording to thespecific situation.
Step 3: Massage the hair for a fewminutes.
Step 4: Keep the hair dry for severalhoursbefore doing other treatments.

DOSAGE

Use biotin hair growth essencehair growth spray for 1-3 monthsto improve hair and beard |prevent white hair environmentand hair loss, and increase itsdensity by 100% within 90 days